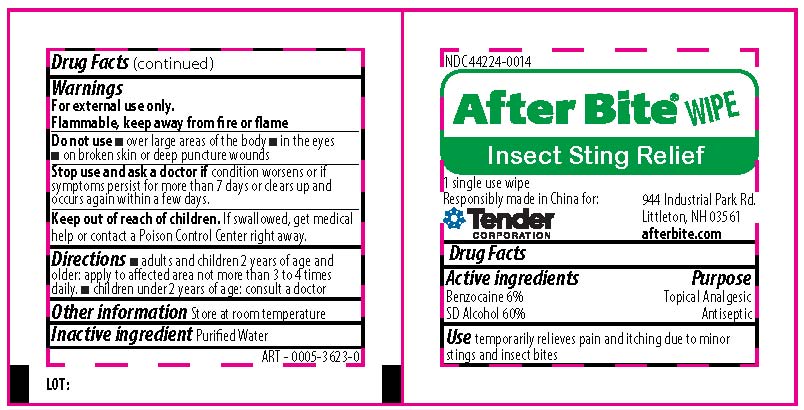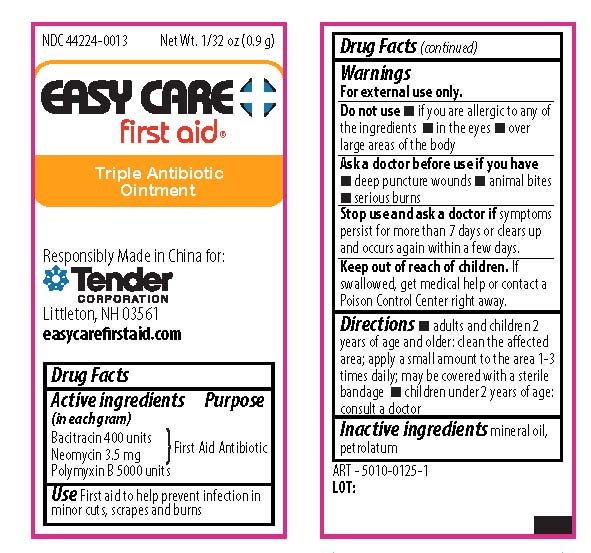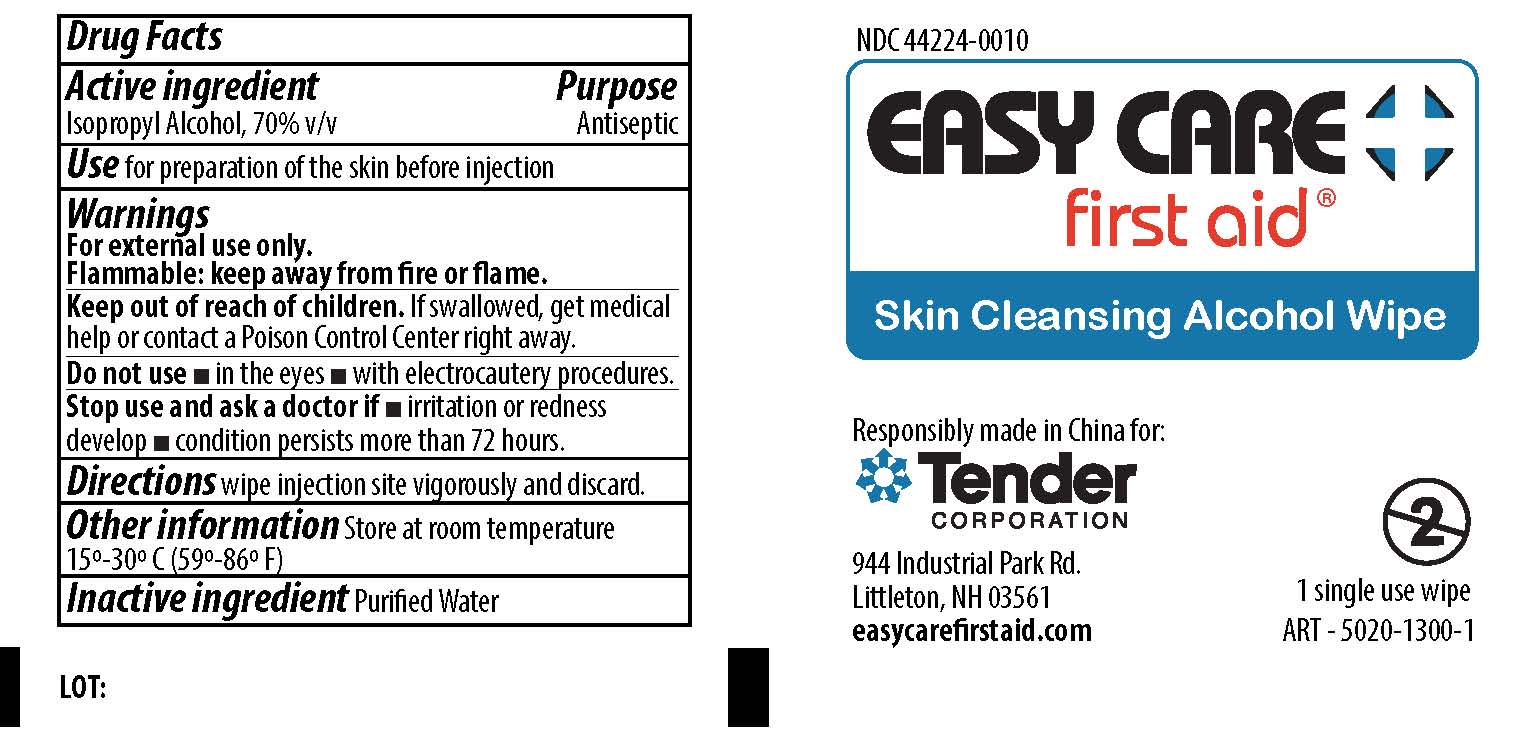 DRUG LABEL: CVS Health Healing on the Go Kit
NDC: 69842-418 | Form: KIT | Route: TOPICAL
Manufacturer: CVS Pharmacy Inc
Category: otc | Type: HUMAN OTC DRUG LABEL
Date: 20190930

ACTIVE INGREDIENTS: ISOPROPYL ALCOHOL 70 mL/100 mL; BACITRACIN ZINC 400 [iU]/1 g; POLYMYXIN B SULFATE 5000 [iU]/1 g; NEOMYCIN SULFATE 5 mg/1 g; BENZOCAINE 6 mg/100 mg; ALCOHOL 60 mg/100 mg
INACTIVE INGREDIENTS: WATER; PETROLATUM; MINERAL OIL; WATER

CVS Health Healing on the Go Kit

Active Ingredient

Isopropyl Alcohol, 70% v/v

Purpose

Antiseptic

Use

For preparation of skin before injection.

Warnings

For external use only.

Flammable - keep away from fire or flame

Do not use

- in the eyes
- with electrocautery procedures

Stop use and ask a doctor if

- irritation and redness develop
- condition persists for more than 72 hours

KEEP OUT OF REACH OF CHILDREN

If swallowed, get medical help or contact a Poison Control Center right away.

Directions

Wipe Injection site vigorously and discard.

Other Information

Store at room temperature 15-30 degree Celsius (59-86 degree Fahrenheit)

Inactive Ingredient

purified water

ACTIVE INGREDIENTS

Bacitracin Zinc 400 units

Neomycin Sulfate 5mg (equivalent to 3.5 mg Neomycin base)

Polymyxin B Sulfate 5000 units

PURPOSE

First Aid Antibiotic

USE

First aid to help prevent infection in minor cuts, scrapes, and burns.

WARNINGS

For external use only.

DO NOT USE

- if you are allergic to any of the ingredients
- in the eyes
- over large areas of the body

Ask a doctor before use if you have

- deep pumcture wounds
- animal bites
- serious burns

STOP USE AND ASK A DOCTOR IF

Symptoms persist for more than 7 days or clear up and occur again within a few days.

KEEP OUT OF REACH OF CHILDREN

if swallowed, get medical help or contact a Poison Control Center right away

Directions

- adults and children 2 year of age and older: clean the affected area; apply a small amount to the area 1-3 times daily; may be covered with a sterile bandage
- children under 2 years of age: consult a doctor

Inactive Ingredients

mineral oil, petrolatum

ACTIVE INGREDIENTS

Benzocaine, 6%

SD alcohol, 60%

PURPOSE

Topical Analgesic
Antiseptic

USE

temporarily relieves pain and itching due to minor stings and insect bites

WARNINGS

For external use only.

Flammable, keep away from fire or flame.

DO NOT USE

- over large areas of the body
- in the eyes
- on broken skin or deep puncture wounds

STOP USE AND ASK A DOCTOR IF

condition worsens or if symptoms persist for more than 7 days or clears up and occurs again within a few days.

KEEP OUT OF REACH OF CHILDREN

If swallowed, get medical help or contact a Poison Control Center right away.

DIRECTIONS

- adults and children 2 year of age and older: apply to affected area not more than 3 to 4 times daily.
- children under 2 years of age: consult a doctor

OTHER INFORMATION

Store at room temperature

INACTIVE INGREDIENT

Purified water

PACKAGE LABEL

Easy Care First Aid® Skin Cleansing Alcohol Wipe

Responsibly made in China for:

Tender Corporation

944 Industrial Park Rd.

Littleton, NH 03561
easycarefirstaid.com

1 single use wipe

PRINCIPAL DISPLAY PANEL

Easy Care First Aid

Triple Antibiotic Ointment

Responsibly Made in China for:

Tender Corporation

Littleton, NH 03561

easycarefirstaid.com

PACKAGE LABEL

After Bite Wipe Insect Sting Relief

1 single use wipes

Responsibly made in China for:

Tender Corporation

944 Industrial park Rd.

Littleton, NH

afterbite.com